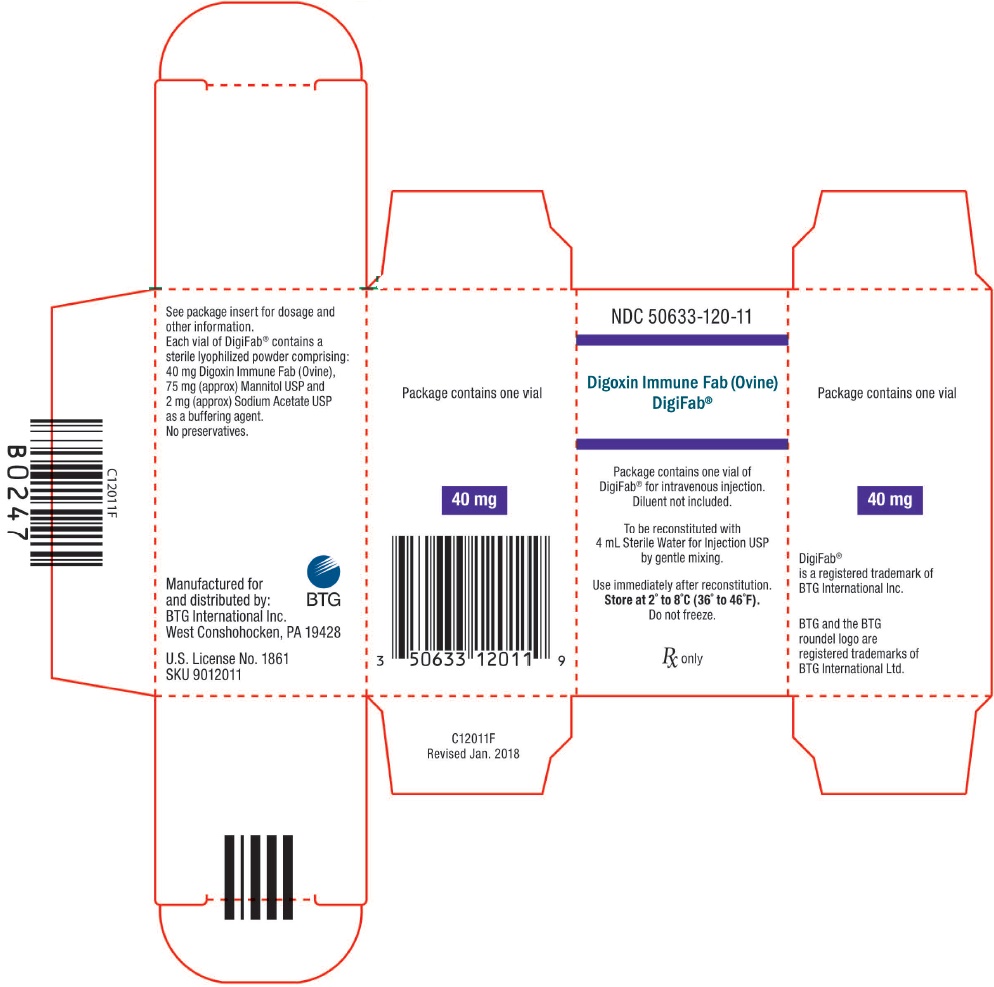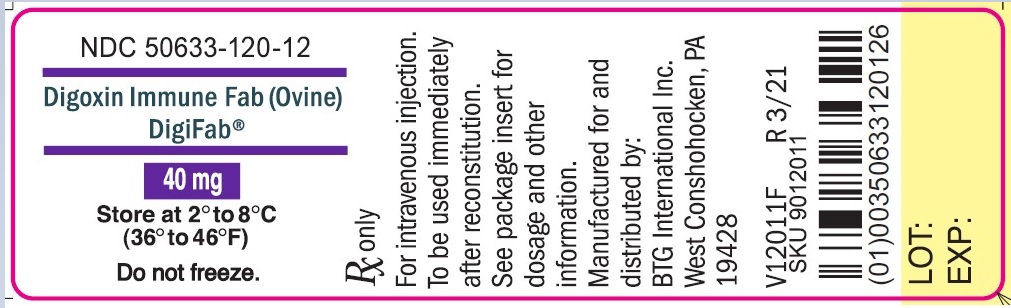 DRUG LABEL: DigiFab
NDC: 50633-120 | Form: INJECTION, POWDER, LYOPHILIZED, FOR SOLUTION
Manufacturer: BTG International Inc.
Category: other | Type: PLASMA DERIVATIVE
Date: 20250124

ACTIVE INGREDIENTS: OVINE DIGOXIN IMMUNE FAB 40 mg/1 1
INACTIVE INGREDIENTS: MANNITOL; SODIUM ACETATE

HIGHLIGHTS OF PRESCRIBING INFORMATION

These highlights do not include all the information needed to use DIGIFAB safely and effectively. See full prescribing information for DIGIFAB.
DigiFab®, Digoxin Immune Fab (Ovine) For Intravenous Injection Only – Lyophilized Powder for Solution
Initial U.S. Approval: 2001

1 INDICATIONS AND USAGE

DIGIFAB is a digoxin immune fab (ovine) and is indicated for treatment of life-threatening or potentially life-threatening digoxin toxicity or overdose.(1)

2 DOSAGE AND ADMINISTRATION

For intravenous use only

Clinical Conditions | Dosage
Acute ingestion of unknown amounts of digoxin and toxicity in the absence of a serum digitalis concentration or estimated ingestion amount | Administer 20 vials of DIGIFAB. Monitor for volume overload in small (< 20 Kg) children. Start with 10 vials followed by an additional 10 vials, if needed, to avoid a febrile reaction.
Chronic digoxin toxicity in the absence of a serum digitalis concentration | Administer 6 vials of DIGIFAB in Adults and Children ≥ 20 Kg. Administer 1 vial of DIGIFAB in Infants and Children < 20 Kg.
Acute ingestion of known amounts of digoxin | Dose (in vials) = Amount of digoxin ingested (in mg) 0.5 mg/vial
Chronic digoxin toxicity and known serum digitalis concentration | Dose (in vials) = (Serum digoxin ng/mL)(weight in kg) 100

3 DOSAGE FORMS AND STRENGTHS

DIGIFAB is supplied as a sterile, lyophilized preparation. Each vial contains 40 mg of digoxin immune fab protein.

5 WARNINGS AND PRECAUTIONS

- Rapid drop in serum potassium concentration after treatment with DIGIFAB. Monitor frequently, especially after the first several hours of DigiFab administration. (5.1)
- Anaphylaxis and hypersensitivity reactions are possible. Patients with allergies to papain, chymopapain, other papaya extracts, or the pineapple enzyme bromelain may be at risk for an allergic reaction to DIGIFAB.
- Clinically misleading reading of standard serum digoxin concentration may occur after administration of DIGIFABdue to interference with digitalis immunoassay measurements. (5.4)

6 ADVERSE REACTIONS

The most common adverse reactions (>7%) are worsening congestive heart failure (13%), hypokalemia (13%) and worsening atrial fibrillation (7%). (6)

To report SUSPECTED ADVERSE REACTIONS, contact BTG 1-877-377-3784, or FDA at 1-800-FDA-1088 or www.fda.gov/medwatch.

8 USE IN SPECIFIC POPULATIONS

- Pregnancy: No human or animal data. Use only if clearly needed. (8.1)

FULL PRESCRIBING INFORMATION

1 INDICATIONS AND USAGE

DIGIFAB is indicated for the treatment of patients with life-threatening or potentially life-threatening digoxin toxicity or overdose, including:

- Known suicidal or accidental consumption of fatal doses of digoxin: 10 mg or more of digoxin in healthy adults, or 4 mg (or more than 0.1 mg/kg) in healthy children, or ingestion of an amount that can cause steady state serum concentrations of ≥10 ng/mL;
- Chronic ingestions causing steady-state serum digoxin concentrations >6 ng/mL in adults or 4 ng/mL in children;
- Manifestations of life-threatening toxicity of digoxin overdose such as severe ventricular arrhythmias, progressive bradycardia, and second or third degree heart block not responsive to atropine, serum potassium levels exceeding 5.5 mEq/L in adults or 6 mEq/L in children with rapidly progressive signs and symptoms of digoxin toxicity.

2 DOSAGE AND ADMINISTRATION

For Intravenous Use Only

2.1 Dosage

General Guidelines:
Adjust the dosage of DIGIFAB according to the amount of digoxin to be neutralized.

Summary of Dosing Guidelines
Clinical Conditions | Dosage
Acute ingestion of unknown amounts of digoxin and toxicity in the absence of a serum digitalis concentration or estimated ingestion amount | Administer 20 vials of DIGIFAB. Monitor for volume overload in small (<20 Kg) children. Start with 10 vials followed by an additional 10 vials, if needed, to avoid a febrile reaction.
Chronic digoxin toxicity in the absence of a serum digitalis concentration | Administer 6 vials of DIGIFAB in Adults and Children ≥ 20 Kg. Administer 1 vial of DIGIFAB in Infants and Children < 20 Kg.
Acute ingestion of known amounts of digoxin | Dose (in vials) = Amount of digoxin ingested (in mg) 0.5 mg/vial
Chronic digoxin toxicity and known serum digitalis concentration | Dose (in vials) = (Serum digoxind ng/mL)(weight in kg) 100

Failure of the patient to respond to DIGIFAB should alert the physician to the possibility that the clinical problem may not be caused by digitalis toxicity.

DOSAGE CALCULATION

General

Methods for calculating a neutralizing dose of DIGIFAB, based on a known or estimated amount of digoxin or digitoxin in the body, are provided below. When using the dose calculation methods provided, the following guidelines should be considered:

- Inaccurate estimates of the amount of digitalis ingested or absorbed may occur due to non-steady state serum concentrations or due to digitalis assay limitations. Most serum digoxin assay kits are designed to measure concentrations less than 5 ng/mL; therefore, sample dilution is required to accurately measure serum concentrations > 5 ng/mL.
- Dosage calculations are based on a steady state volume of distribution of approximately 5 L/kg for digoxin, which is used to convert serum digoxin concentrations to total body burden of digoxin in milligrams. The volume of distribution is a population average and may vary among individuals. Many patients may require higher doses for complete neutralization and doses should usually be rounded up to the nearest whole vial.
- If toxicity has not adequately reversed after several hours, or appears to recur, re-administration of DIGIFAB, at a dose guided by clinical judgment, may be necessary. If a patient is in need of re-administration of DIGIFAB due to recurrent toxicity, or to a new toxic episode that occurs soon after the first episode, measurement of free (unbound) serum digitalis concentrations should be considered since Fab may still be present in the body.
- Failure of a patient to respond to DIGIFAB treatment may indicate that the clinical problem is not caused by digitalis intoxication. If there is no response to an adequate dose of DIGIFAB, the diagnosis of digitalis toxicity should be questioned.

Calculation for Ingestion of Known Amount:

- Each vial of DIGIFAB (40 mg of purified digoxin-specific Fab) binds approximately 0.5 mg of digoxin.
- The total number of vials required can be calculated by dividing the total body load of digoxin in milligrams (mg) by 0.5 mg per vial (see Formula 1).
- Following an acute ingestion, total body load will be approximately equal to the amount ingested in milligrams for either digoxin capsules or digitoxin.
- In case of digoxin tablet ingestion , the total body load will be approximately equal to the amount ingested (in mg) multiplied by the bioavailability of the tablet preparation, which is 0.8.

Table 1 gives dosage estimates in number of vials for adults and children who have ingested a single large dose of digoxin and for whom the approximate number of tablets or capsules is known. The dose of DIGIFAB (in number of vials) represented in Table 1 can be approximated using the following formula:

Formula 1

Dose = total digitalis body load in mg
(in # of vials) 0.5 mg of digitalis bound/vial

Table 1 Approximate Dose of DIGIFAB for Reversal of a Single Large Digoxin Overdose
Number of Digoxin Tablets or Capsules Ingested* | Dose of DIGIFAB # of vials
25 | 10
50 | 20
75 | 30
100 | 40
150 | 60
200 | 80
*0.25 mg tablets with 80% bioavailability or 0.2 mg capsules with 100% bioavailability

If, after several hours, toxicity is not adequately reversed, or appears to recur, additional administration of DIGIFAB at a dose guided by clinical judgment may be required.

Calculations Based on Steady-State Serum Digoxin Concentrations:

Adults

Table 2 gives dosage estimates in number of vials for adult patients for whom a steady-state serum digoxin concentration is known. The dose of DIGIFAB (in number of vials) represented in Table 2 can be approximated using the following formula:

Formula 2 (see Table 2)

Dose = (Serum digoxin concentration in ng/mL)(weight in kg)
(in # of vials) 100

Table 2 Adult Dose Estimate of DIGIFAB (in # of vials) from Steady-State Serum Digoxin Concentration
Patient Weight (kg) | Serum Digoxin Concentration (ng/mL)
 | 1 | 2 | 4 | 8 | 12 | 16 | 20
40 | 0.5v | 1v | 2v | 3v | 5v | 7v | 8v
60 | 0.5v | 1v | 3v | 5v | 7v | 10v | 12v
70 | 1v | 2v | 3v | 6v | 9v | 11v | 14v
80 | 1v | 2v | 3v | 7v | 10v | 13v | 16v
100 | 1v | 2v | 4v | 8v | 12v | 16v | 20v
v = vials

Children:

- Table 3 gives dosage estimates in milligrams for infants and small (< 20 Kg) children based on the steady-state serum digoxin concentration.
- The dose of DIGIFAB represented in Table 3 can be estimated by multiplying the dose (in number of vials) calculated from Formula 2 by the amount of DIGIFAB contained in a vial (40 mg/vial) (see Formula 3).
- Administer smaller doses in children < 20 Kg requiring doses < 1mL with a tuberculin syringe after reconstituting 40 mg.
- For very small doses, a reconstituted vial can be diluted with 36 mL of sterile isotonic saline to achieve a concentration of 1 mg/mL.

Formula 3 (see Table 3)

Dose (in mg) = (Dose in # of vials) (40 mg/vial)

Table 3 Infants and Small (< 20 Kg) Children Dose Estimates of DIGIFAB (in mg) from Steady State Serum Digoxin Concentration
Patient Weight (kg) | Serum Digoxin Concentration (ng/mL)
 | 1 | 2 | 4 | 8 | 12 | 16 | 20
1 | 0.4 mg* | 1 mg* | 1.5 mg* | 3 mg* | 5 mg | 6.5 mg | 8 mg
3 | 1 mg* | 2.5 mg* | 5 mg | 10 mg | 14 mg | 19 mg | 24 mg
5 | 2 mg* | 4 mg | 8 mg | 16 mg | 24 mg | 32 mg | 40 mg
10 | 4 mg | 8 mg | 16 mg | 32 mg | 48 mg | 64 mg | 80 mg
20 | 8 mg | 16 mg | 32 mg | 64 mg | 96 mg | 128 mg | 160 mg
* dilution of reconstituted vial to 1 mg/mL may be desirable

Calculation Based on Steady-State Digitoxin Concentrations:

The dose of DIGIFAB for digitoxin toxicity can be approximated by using the following formula (which differs from Formula 2 in the denominator due to a 10-fold decrease in the volume of distribution of digitoxin as compared to digoxin).

Formula 4

Dose = (Serum digitoxin concentration in ng/mL) (weight in kg)
(in # of vials) 1000

If in any case, the dose estimated based on ingested amount (Formula 1) differs substantially from that calculated based on the serum digoxin or digitoxin concentration (Formulas 2 and 4), it may be preferable to use the higher dose estimate.

2.2 Preparation and Administration

- Each vial contains 40 mg of digoxin immune Fab protein and is intended for one time use only as it contains no preservatives
- Reconstitute each vial of DIGIFAB with 4 mL of Sterile Water for Injection USP and gently mix to provide a solution containing approximately 10 mg/mL of digoxin immune Fab protein.
- Use the reconstituted product promptly. If not used immediately, store under refrigeration at 2° to 8°C (36° to 46°F) for up to 4 hours. Add the reconstituted product to an appropriate volume of 0.9% sodium chloride for injection.
- Visually inspect reconstituted vials for particulate matter and discoloration prior to administration, whenever solution and container permit. Do not use if the solution is cloudy, turbid or if it contains particulates.
- Administer DIGIFAB slowly as an intravenous infusion over at least 30 minutes. Stop the infusion if infusion rate-related anaphylactoid-type reactions occur, such as hypotension, wheezing, or urticaria. The infusion can be re-started at a slower rate. Give DIGIFAB by bolus injection, if cardiac arrest is imminent. An increased incidence of infusion-related reactions may be expected with bolus injection.
- For infants and small children who may require very small doses, reconstitute the 40 mg vial as directed and administer undiluted using a tuberculin syringe. For very small doses, a reconstituted vial can be diluted with an additional 36 mL of isotonic saline to achieve a concentration of 1 mg/mL.

3 DOSAGE FORMS AND STRENGTHS

DIGIFAB is supplied as a sterile, purified, lyophilized preparation containing 40 mg of digoxin immune Fab protein per vial.

4 CONTRAINDICATIONS

There are no known contraindications to the use of DIGIFAB.

5 WARNINGS AND PRECAUTIONS

5.1 General

Suicidal ingestion may result from more than one drug. Toxic effects of other drugs or poisons should not be overlooked, especially in cases where signs and symptoms of digitalis toxicity are not relieved by administration of DIGIFAB.

Rapid drop in serum potassium concentration may occur after treatment with DIGIFAB. Monitor frequently, especially after the first several hours of DIGIFAB administration (see 5.4 Laboratory Tests).

Patients with poor cardiac function may deteriorate secondary to the withdrawal of the inotropic action of digoxin by DIGIFAB. If needed, provide additional support by using other intravenous inotropes such as dopamine, dobutamine or vasodilators. However, take additional care not to aggravate the digitalis induced rhythm disturbances. Postpone re-digitalization, if possible, until the Fab fragments have been eliminated from the body, which may require several days, and patients with impaired renal function may require a week or longer.

5.2 Hypersensitivity Reactions

Anaphylaxis and hypersensitivity reactions are possible. Carefully monitor all patients treated with DIGIFAB for signs and symptoms of an acute allergic reaction (e.g., urticaria, pruritus, erythema, angioedema, bronchospasm with wheezing or cough, stridor, laryngeal edema, hypotension, tachycardia) and treat immediately with appropriate emergency medical care (e.g., oxygen, diphenhydramine, corticosteroids, volume expansion and airway management), if one occurs.

If an anaphylactic reaction occurs during the infusion, terminate DIGIFAB administration at once and administer appropriate treatment. Balance the need for epinephrine against its potential risk in the setting of digitalis toxicity. Patients with known allergies to sheep protein are particularly at risk for an anaphylactic reaction, as are individuals who have previously received intact ovine antibodies or ovine Fab.

Do not administer DIGIFAB to patients with a known history of hypersensitivity to papaya or papain unless the benefits outweigh the risks and appropriate management for anaphylactic reactions is readily available. Prior treatment with digoxin-specific ovine immune Fab carries a theoretical risk of sensitization to ovine serum protein and possible diminution of the efficacy of the drug due to the presence of human antibodies against ovine Fab. To date, there have been no clinical reports of human anti-ovine immunoglobulin antibodies causing a reduction in binding of ovine digoxin immune Fab or neutralization response to ovine digoxin immune Fab.

5.3 Use of DIGIFAB in Renal Failure

The elimination half-life of DIGIFAB in renal failure has not been clearly defined. Monitor patients with severe renal failure who receive DIGIFAB for digitalis toxicity for a prolonged period for possible recurrence of toxicity.

Monitoring of free (unbound) digoxin concentrations after the administration may be appropriate in order to establish recrudescent toxicity in renal failure patients. ^5

5.4 Laboratory Tests

DIGIFAB may interfere with digitalis immunoassay measurements. Thus, standard serum digoxin concentration measurements may be clinically misleading until the Fab fragments are eliminated from the body. This may take several days or a week or more in patients with markedly impaired renal function. Therefore, serum samples for digoxin concentration should be obtained before DIGIFAB administration, if at all possible. Such measurements would establish the level of serum digoxin at the time of diagnosis of digitalis intoxication.

At least 6 to 8 hours are required for equilibration of digoxin between serum and tissue, so absorption of the last dose may continue from the intestine. Therefore, serum measurements may be difficult to interpret if samples are drawn soon after the last digitalis dose.

The total serum digoxin concentration may rise precipitously following administration of DIGIFAB, but this will be almost entirely bound to the Fab fragment and therefore not able to react with receptors in the body.

Patients should be closely monitored, including temperature, blood pressure, electrocardiogram, and potassium concentration, during and after administration of DIGIFAB. Digoxin causes a shift of potassium from inside to outside the cell, such that severe intoxication can cause a life-threatening elevation of serum potassium. This may lead to increased urinary excretion of potassium so that a patient may have hyperkalemia but a whole body deficit of potassium. When the toxic effects of digoxin are reversed by DIGIFAB, potassium shifts back into the cell with a resulting decline in serum potassium concentration. This hypokalemia may develop rapidly. For these reasons, serum potassium concentration should be followed closely, especially during the first several hours after DIGIFAB administration. Cautious potassium supplementation should then be given when necessary.

6 ADVERSE REACTIONS

The most common adverse reactions (> 7%) related to DIGIFAB administration are worsening congestive heart failure (13%), hypokalemia (13%) and worsening atrial fibrillation (7%).

6.1 Clinical Trial Experience

Because clinical trials are conducted under widely varying conditions, adverse reaction rates observed in the clinical trials of a drug cannot be directly compared to rates in the clinical trials of another drug and may not reflect the rates observed in clinical practice.

In the clinical trials of DIGIFAB, 6 of 15 patients in the digoxin overdose study had a total of 17 adverse events. Three events occurred in one patient and consisted of the following: pulmonary edema, bilateral pleural effusion and renal failure. The events were determined to be likely due to the loss of digoxin inotropic support in combination with the patient’s underlying medical condition. Of 8 healthy volunteers who received DIGIFAB, two experienced an adverse reaction that was considered to be related to DIGIFAB. The reactions were; one episode of phlebitis of the infusion-site vein and one episode of transient postural hypotension.

8 USE IN SPECIFIC POPULATIONS

8.1 Pregnancy

Risk Summary
Animal reproduction studies have not been conducted with DIGIFAB. It is also not known whether DIGIFAB can cause fetal harm when administered to a pregnant woman or can affect reproduction capacity. DIGIFAB should be given to a pregnant woman only if clinically needed.

8.2 Lactation

Risk Summary
It is not known whether DIGIFAB is excreted in human breast milk. Because many drugs are excreted in human milk, caution should be exercised when DIGIFAB is administered to a nursing woman. DIGIFAB should be given to nursing mothers only if clinically needed.

8.4 Pediatric Use

Safety data in pediatric population is limited. The pediatric dosing estimation is based on calculations for adult dosing.

8.5 Geriatric Use

Specific studies in elderly patients have not been conducted. Of the 15 patients given DIGIFAB for digoxin toxicity in one clinical trial, the average age of all patients was 64 years and over half of the patients (8 of the 15) were 65 years of age or older. The oldest patient studied was 86 years old. There is no evidence that the efficacy of DIGIFAB would be altered due to advanced age alone; however, elderly patients have a higher chance of having impaired renal function and therefore should be monitored more closely for recurrent toxicity (See 5.3 Use of DIGIFAB in renal failure).

11 DESCRIPTION

DIGIFAB [Digoxin Immune Fab (Ovine)] is a sterile, lyophilized preparation of digoxin-immune ovine Fab (monovalent) immunoglobulin fragments. These fragments are obtained from the blood of healthy sheep immunized with a digoxin derivative, digoxin-dicarboxymethoxylamine (DDMA), a digoxin analogue which contains the functionally essential cyclopentaperhydrophenanthrene: lactone ring moiety coupled to keyhole limpet hemocyanin (KLH).

The final product is prepared by isolating the immunoglobulin fraction of the ovine serum, digesting it with papain and isolating the digoxin-specific Fab fragments by affinity chromatography. These antibody fragments have a molecular weight of approximately 46,000 Da.

Each vial of DIGIFAB, which will bind approximately 0.5 mg digoxin, contains 40 mg of digoxin immune Fab, 75 mg (approx) of mannitol USP, and 2 mg (approx) sodium acetate USP as a buffering agent.

The product contains no preservatives and is intended for intravenous administration after reconstitution with 4 mL of Sterile Water for Injection USP.

12 CLINICAL PHARMACOLOGY

12.1 Mechanism of Action

DIGIFAB has an affinity for digoxin in the range of 10^9 to 10^10 M^-1, which is greater than the affinity of digoxin for its sodium pump receptor, the presumed receptor for its therapeutic and toxic effects. When administered to the intoxicated patient, DIGIFAB binds to molecules of digoxin reducing free digoxin levels, which results in a shift in the equilibrium away from binding to the receptors, thereby reducing cardio-toxic effects. Fab-digoxin complexes are then cleared by the kidney and reticuloendothelial system.

12.3 Pharmacokinetics

The pharmacokinetics and pharmacodynamics of DIGIFAB were assessed in a randomized and controlled study of DIGIFAB and Digibind® (n=8) or Digibind® (n=8). The objective of the pharmacokinetic and pharmacodynamic study was to compare parameters for DIGIFAB to those for Digibind®. and Digibind®, respectively) indicate considerable penetration from the circulation into the extracellular space and are consistent with previous reports of ovine Fab distribution, as are the elimination half-life values (15 hours and 23 hours for DIGIFAB and Digibind®, respectively).^8-12 The elimination half-life of 15-20 hours in patients with normal renal function appears to be increased up to 10 fold in patients with renal impairment, although volume of distribution remains unaffected.^12

The primary outcome measure for this study was the serum level of free (unbound) digoxin. The results demonstrated that both products reduced the level of free digoxin in the serum to below the limit of assay quantitation for several hours after Fab administration. Cumulative urinary excretion of digoxin was comparable for both products and exceeded 40% of the administered dose by 24 hours. These results demonstrate that DIGIFAB and Digibind® have equivalent pharmacodynamic effects on the digoxin parameters that are relevant to the treatment of digoxin toxicity.

13 NONCLINICAL TOXICOLOGY

13.1 Carcinogenesis, Mutagenesis, Impairment of Fertility

Animal carcinogenicity and reproduction studies have not been conducted with DigiFab.

13.2 Animal Toxicology and/or Pharmacology

No toxic effects were observed when DIGIFAB was administered to healthy male Sprague Dawley rats in equimolar doses sufficient to neutralize a 1 mg/kg dose of digoxin. In these studies, the physiologic changes produced by toxic serum concentrations of digoxin were ameliorated rapidly by the administration of DIGIFAB or comparator product Digibind®. Statistically equivalent responses were observed with both DIGIFAB and Digibind® to the following variables: PTQ index, heart rate, mean arterial pressure, ventilation, arterial blood gases, and serum potassium concentrations.

14 CLINICAL STUDIES

One prospective multi-center safety, efficacy and pharmacokinetic study in patients presenting with life-threatening digoxin toxicity was conducted in U.S. and Finland.

The objective of the study was to demonstrate safety, pharmacokinetics, and clinical response of DIGIFAB in patients. Results were compared to historical data on Digibind ®. Fifteen patients received doses of DIGIFAB based on its theoretical binding capacity for digoxin, and based on the known amount of digoxin ingested or on blood concentrations of digoxin at the time of admission.

Serum free digoxin concentrations fell to undetectable concentrations in all patients following DIGIFAB administration. Ten of the 15 patients studied who had baseline ECG abnormalities improved within 4 hours after the DIGIFAB infusion. The remaining 5 patients who had baseline ECG abnormalities remained unchanged throughout the 24-hour assessment period, and in one case through the 30-day follow up period. Seven out of the 15 patients (47%) studied had complete resolution of digoxin toxicity within 4 hours of DIGIFAB administration, and 14 patients (93%) were classified as having resolved their digoxin toxicity by 20 hours. In this study, where 2/15 patients had serum available for human anti-ovine antibody determination, there was no measurable immune response.

15 REFERENCES

1. Kojis FG. Serum sickness and anaphylaxis: analysis of cases of 6,211 patients treated with horse serum for various infections. Am J Dis Children 1942; 64:93-143, 313-350.
2. Quarre JP, Lecomte J, Lauwers D, Gilbert P, Thiriaux J. Allergy to latex and papain. J Allergy Clin Immunol 1995; 95(4):922.
3. Baur X, Chen Z, Rozynek P, Düser D, Raulf-Heimsoth M. Cross-reacting IgE antibodies recognizing latex allergens, including Hev b 1, as well as papain. Allergy 1995; 50(7):604-609.
4. Wenger TL. Experience with digoxin immune fab (ovine) in patients with renal impairment. Am J of Emer Med 1991; 9(supp. 1):21-23.
5. Valdes R, Jortani SA. Monitoring of unbound digoxin in patients with antidigoxin antigen-binding fragments: a model for the future ? Clin Chem 1998; 44(9):1883-1885.
6. Kirkpatrick CHG, Digibind® Study Advisory Panel. Allergic histories and reactions of patients treated with digoxin immune fab (ovine) antibody. Am J of Emer Med 1991; 9(supp. 1):7-10.
7. Ward, SB, Sjostrom L, and Ujhelyi MR. Comparison of the pharmacokinetics and in vivo binding affinity of DigiTAb versus Digibind.Therapeutic Drug Monitoring 2000; 22:599-607.
8. Hickey AR, Wenger TL, Carpenter VP, et al. Digoxin immune fab therapy in the management of digitalis intoxication: safety and efficacy results of an observational surveillance study. J Am Coll Cardiol 1991; 17:590-598.
9. Antman EM, Wenger TL, Butler VP, Haber E, and Smith TW. Treatment of 150 cases of life threatening digitalis intoxication with digoxin-specific fab antibody fragments. Circulation 1990; 81:1744-1752.
10. Wenger TL, Butler VP Jr, Haber E, Smith TW. Treatment of 63 severely digitalis-toxic patients with digoxin-specific antibody fragments. J Am Coll Cardiol 1985; 5 (supp.):118A-123A.
11. Schaumann W, Kaufmann B, Neubert P, Smolarz A. Kinetics of the fab fragments of digoxin antibodies and of bound digoxin in patients with severe digoxin intoxication. Eur J Clin Pharmacol 1986; 30:527-533.
12. Ujhelyi MR, Robert S. Pharmacokinetic aspects of digoxin-specific fab therapy in the management of digitalis toxicity. Clin Pharmacokinet 1995; 28(6):483-493.

16 HOW SUPPLIED/STORAGE AND HANDLING

DigiFab is supplied as a carton that contains 1 vial of product (diluent not included).

- NDC 50633-120-11
- Store at 2° to 8°C (36° to 46°F).
- Do not freeze.
- Use within 4 hours after reconstitution.

17 PATIENT COUNSELING INFORMATION

Advise patients to contact their physician immediately if they experience any signs and symptoms of delayed allergic reactions or serum sickness (e.g., rash, pruritus, urticaria) after hospital discharge.

Manufactured for
and distributed by:

BTG International Inc.
West Conshohocken, PA 19428

U.S. License No. 1861

DIGIFAB is a registered trademark of BTG International Inc.
BTG and the BTG roundel logo are registered trademarks of BTG International Ltd.

P12011E